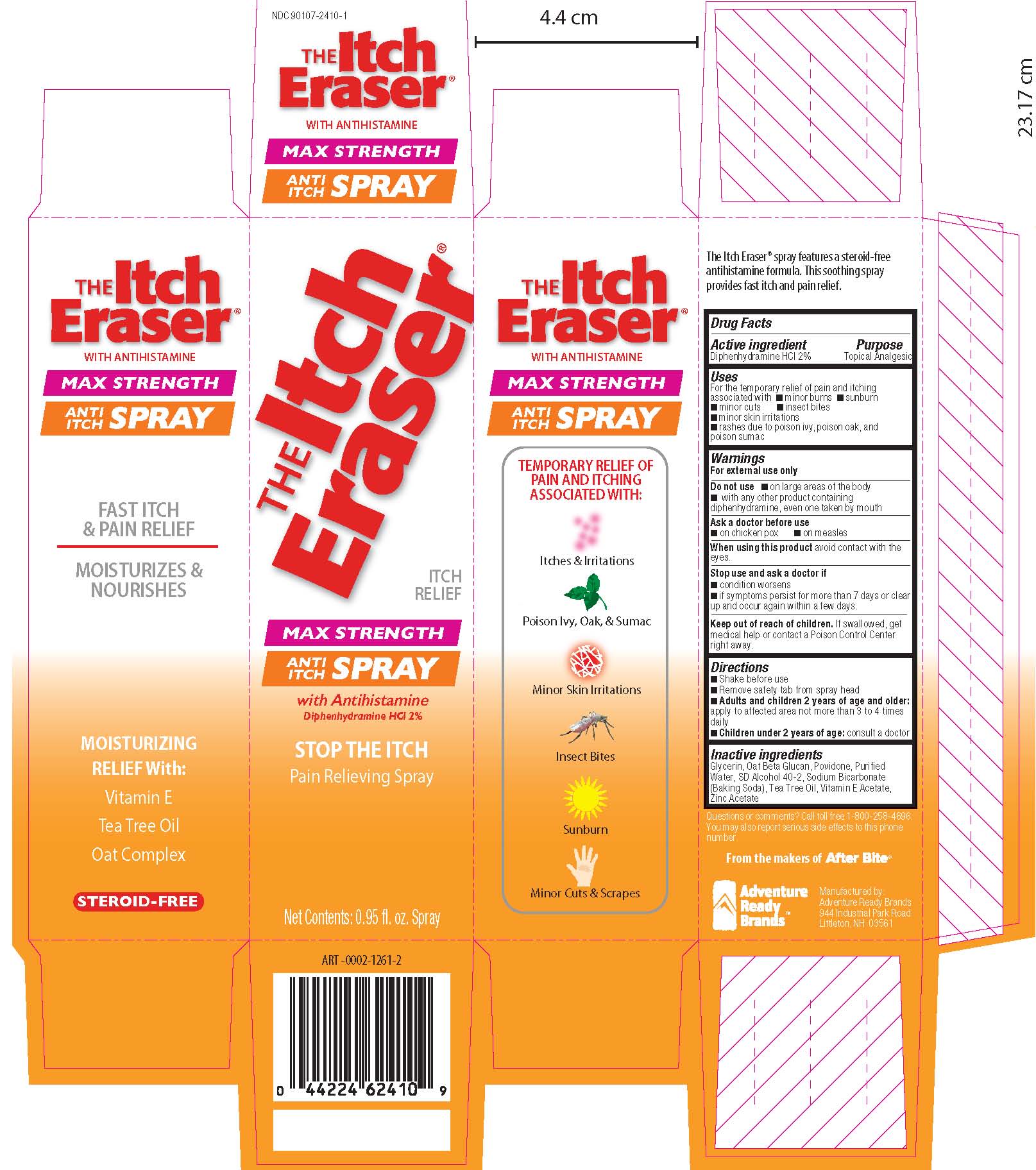 DRUG LABEL: The Itch Eraser
NDC: 90107-2410 | Form: SPRAY
Manufacturer: Adventure Ready Brands
Category: otc | Type: HUMAN OTC DRUG LABEL
Date: 20230119

ACTIVE INGREDIENTS: DIPHENHYDRAMINE HYDROCHLORIDE 20 mg/1 mL
INACTIVE INGREDIENTS: OAT; ALCOHOL; WATER; POVIDONE; GLYCERIN; SODIUM BICARBONATE; .ALPHA.-TOCOPHEROL ACETATE; TEA TREE OIL; ZINC ACETATE

The Itch Eraser Spray

Active ingredients:

Diphenhydramine HCl 2%

Purpose:

Topical analgesic

Uses

For temporary relief of pain and itching associated with:

• minor burns

• sunburn

• minor cuts

• insect bites

• minor skin irritations

• rashes due to poison ivy, poison oak, and poison sumac

Warnings

For external use only

Do not use

• on large areas of the body

• with any other product containing diphenhydramine, even one taken by mouth

Ask a doctor before use

• on chicken pox • on measles

When using this product

avoid contact with the eyes.

Stop use and ask a doctor if

• condition worsens • symptoms last more than 7 days or clear up and occur again within a few days

Keep out of reach of children.

If swallowed, get medical help or contact a Poison Control Center right away.

Directions

- do not use more often than directed
- adults and children 2 years of age and older: apply to affected area not more than 3 to 4 times daily.
- children under 2 years of age: ask a doctor.

Inactive Ingredients

Glycerin, Oat Beta Glucan, Povidone, Purified Water, SD Alcohol 40-2, Sodium Bicarbonate (Baking Soda), Tea Tree Oil, Vitamin E Acetate, Zinc Acetate